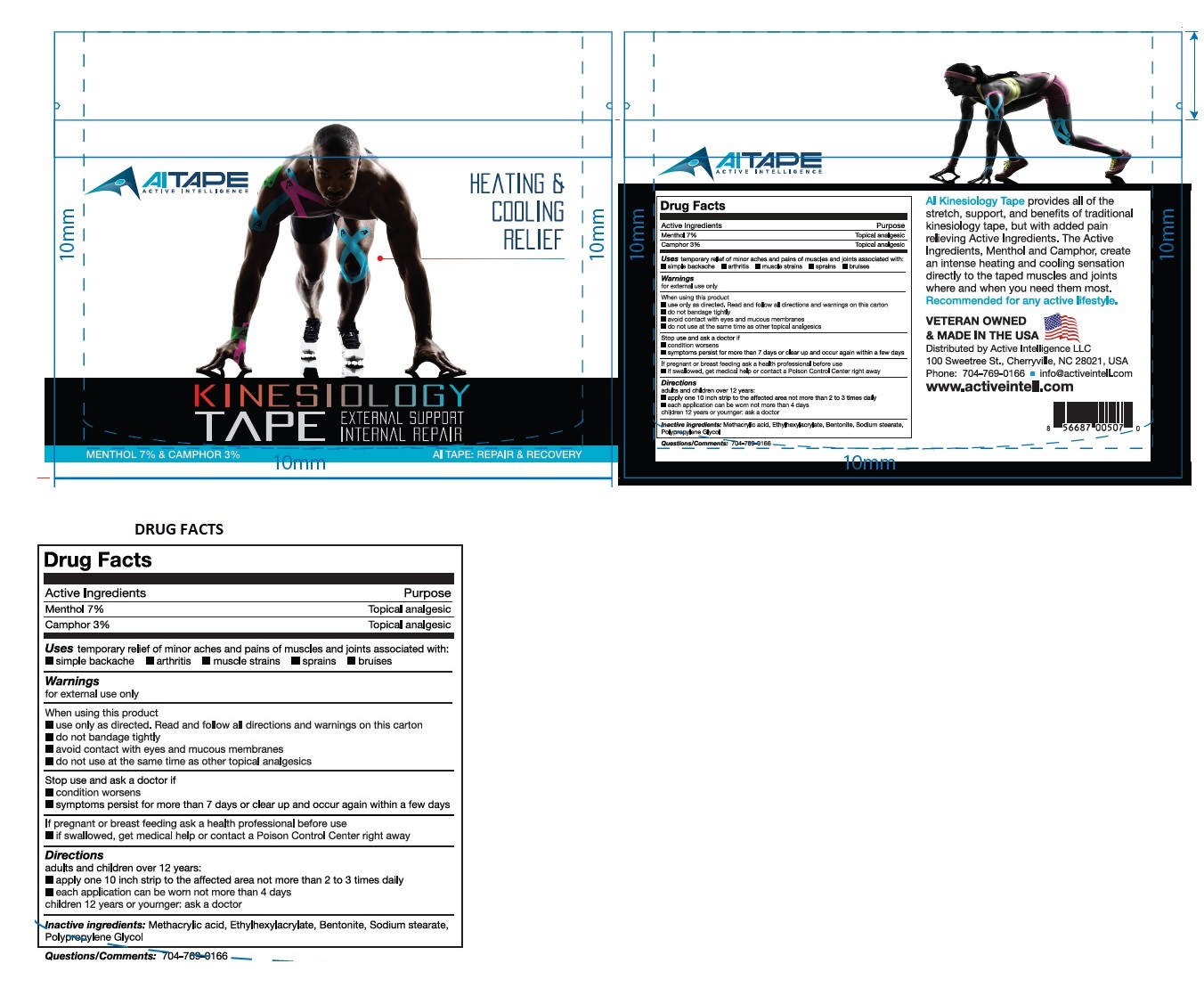 DRUG LABEL: AI Tape
NDC: 71590-010 | Form: TAPE
Manufacturer: Active Intelligence, Llc
Category: otc | Type: HUMAN OTC DRUG LABEL
Date: 20180528

ACTIVE INGREDIENTS: MENTHOL, UNSPECIFIED FORM 7 g/100 g; CAMPHOR (SYNTHETIC) 3 g/100 g
INACTIVE INGREDIENTS: METHACRYLIC ACID; 2-ETHYLHEXYL ACRYLATE; BENTONITE; SODIUM STEARATE; PPG-26 OLEATE

AI Tape

Active Ingredients

Menthol 7%

Camphor 3%

Purpose

Topical analgesic

Uses

temporary relief of minor aches and pains of muscles and joints associated with:

- simple backache • arthritis • muscle strains • sprains • bruises

Warnings

for external use only.

When using this product

- use only as directed. Read and follow all directions and warnings on this carton
- do not bandage tightly
- avoid contact with eyes and mucous membranes
- do not use at the same time as other topical analgesics

Stop use and ask a doctor if

- condition worsens
- symptoms persist for more than 7 days or clear up and occur again within a few days

If pregnant or breast feeding ask a health professional before use

KEEP OUT OF REACH OF CHILDREN

- if swallowed, get medical help or contact a Poison Control Center right away

Directions

adults and children over 12 years:

• apply one 10 inch strip to the affected area not more than 2 to 3 times daily

• each application can be worn not more than 4 day

children 12 years or younger:ask a doctor

Inactive ingredients:

Methacrylic acid, Ethylhexylacrylate, Bentonite, Sodium stearate, Polypropylene Glycol.

Questions /Comments:

704-769-0166

HEATING & COOLING RELIEF

KINESIOLOGY TAPE

EXTERNAL SUPPORT INTERNAL REPAIR

AI TAPE: REPAIR & RECOVERY

AI Kinesiology Tape provides all of the stretch, support and benefits of traditional Kinesiology tape, but with added pain relieving Active Ingredients. The Active Ingredients Menthol and Camphor, create an intense heating and cooling sensation directly to the taped muscles and joints where and when you need them most.

Recommended for any active lifestyle.

VETERAN OWNED & MADE IN THE USA

Distributed by Active Intelligence LLC

100 Sweetree St,. Cherryville, NC 28021, USA

Phone: 704-769-0166

info@activeintell.com

www.activeintell.com